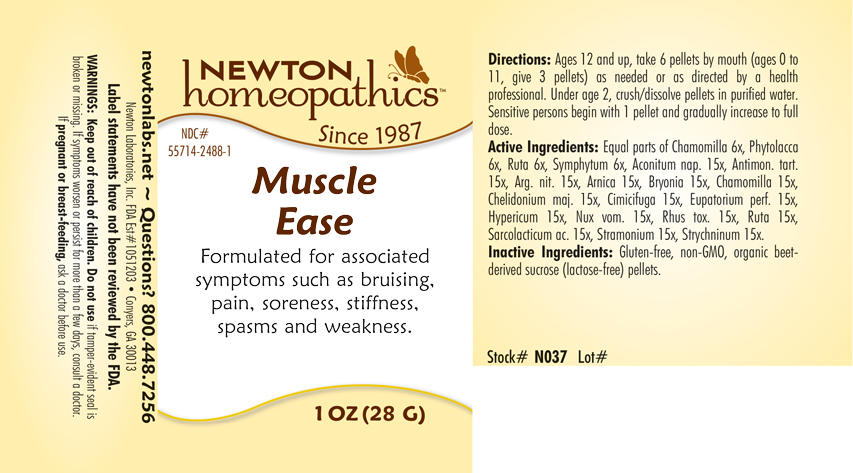 DRUG LABEL: Muscle Ease
NDC: 55714-2488 | Form: PELLET
Manufacturer: Newton Laboratories, Inc.
Category: homeopathic | Type: HUMAN OTC DRUG LABEL
Date: 20250211

ACTIVE INGREDIENTS: COMFREY ROOT 6 [hp_X]/1 g; ACONITUM NAPELLUS 15 [hp_X]/1 g; ANTIMONY POTASSIUM TARTRATE 15 [hp_X]/1 g; SILVER NITRITE 15 [hp_X]/1 g; ARNICA MONTANA 15 [hp_X]/1 g; BRYONIA ALBA ROOT 15 [hp_X]/1 g; CHELIDONIUM MAJUS 15 [hp_X]/1 g; BLACK COHOSH 15 [hp_X]/1 g; EUPATORIUM PERFOLIATUM FLOWERING TOP 15 [hp_X]/1 g; MATRICARIA CHAMOMILLA 15 [hp_X]/1 g; STRYCHNOS NUX-VOMICA SEED 15 [hp_X]/1 g; TOXICODENDRON PUBESCENS LEAF 15 [hp_X]/1 g; RUTA GRAVEOLENS FLOWERING TOP 15 [hp_X]/1 g; LACTIC ACID, L- 15 [hp_X]/1 g; DATURA STRAMONIUM 15 [hp_X]/1 g; STRYCHNINE 15 [hp_X]/1 g; PHYTOLACCA AMERICANA ROOT 6 [hp_X]/1 g; HYPERICUM PERFORATUM 15 [hp_X]/1 g
INACTIVE INGREDIENTS: SUCROSE

Muscle 2488P

INDICATIONS & USAGE SECTION

Formulated for associated symptoms such as bruising, pain, soreness, stiffness, spasms and weakness..

DOSAGE & ADMINISTRATION SECTION

Directions: Ages 12 and up, take 6 pellets by mouth (ages 0 to 11, give 3 pellets) as needed or as directed by a health professional. Under age 2, crush/dissolve pellets in purified water. Sensitive persons begin with 1 pellet and gradually increase to full dose.

OTC - ACTIVE INGREDIENT SECTION

Equal parts of Chamomilla 6x, Phytolacca decandra 6x, Ruta graveolens 6x, Symphytum officinale 6x, Aconitum napellus 15x, Antimonium tartaricum 15x, Argentum nitricum 15x, Arnica montana 15x, Bryonia 15x, Chamomilla 15x, Chelidonium majus 15x, Cimicifuga racemosa 15x, Eupatorium perfoliatum 15x, Hypericum perforatum 15x, Nux vomica 15x, Rhus toxicodendron 15x, Ruta graveolens 15x, Sarcolacticum acidum 15x, Stramonium 15x, Strychninum 15

OTC - PURPOSE SECTION

Formulated for associated symptoms such as bruising, pain, soreness, stiffness, spasms and weakness.

INACTIVE INGREDIENT SECTION

Inactive Ingredients: Gluten-free, non-GMO, organice beet-derived sucrose (lactose-free) pellets.

QUESTIONS SECTION

newtonlabs.net – Questions? 800.448.7256

Newton Laboratories, Inc. FDA Est # 1051203 - Conyers, GA 30013

WARNINGS SECTION

WARNINGS: Keep out of reach of children. Do not use if tamper-evident seal is broken or missing. If symptoms worsen or persist for more than a few days, consult a doctor. If pregnant or breast-feeding, ask a doctor before use.

OTC - PREGNANCY OR BREAST FEEDING SECTION

If pregnant or breast-feeding, ask a doctor before use.

OTC - KEEP OUT OF REACH OF CHILDREN SECTION

Keep out of reach of children.